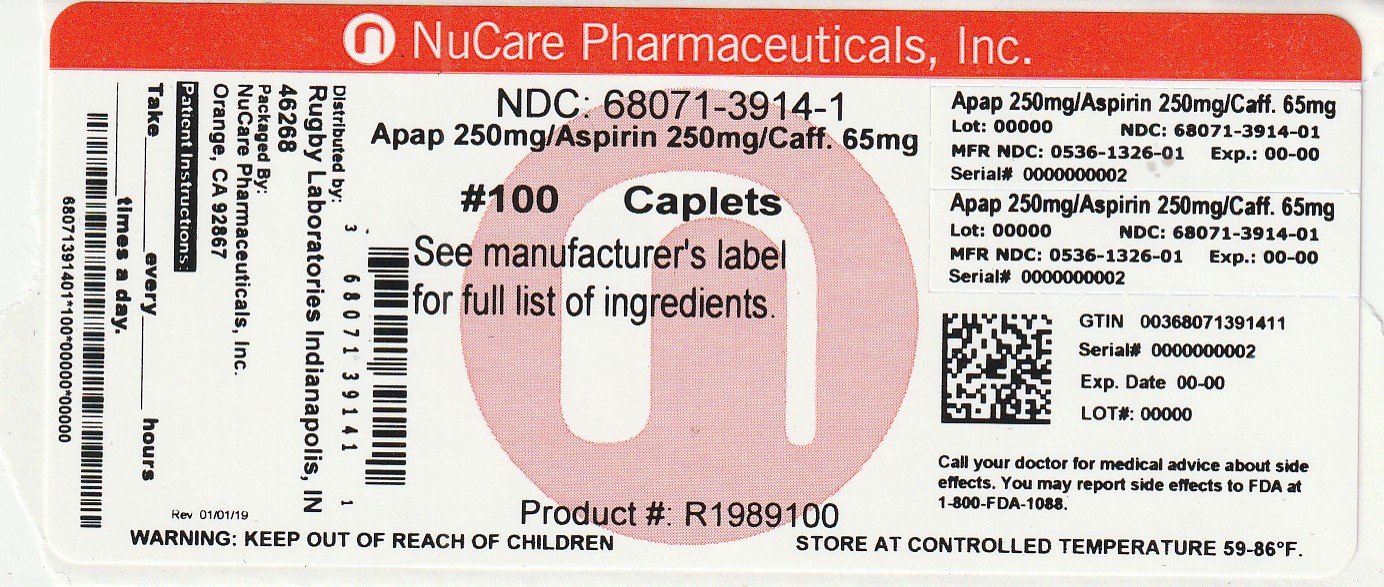 DRUG LABEL: Acetaminophen, Aspirin, Caffeine
NDC: 68071-3914 | Form: TABLET, FILM COATED
Manufacturer: NuCare Pharmaceuticals,Inc.
Category: otc | Type: HUMAN OTC DRUG LABEL
Date: 20251113

ACTIVE INGREDIENTS: ASPIRIN 250 mg/1 1; CAFFEINE 65 mg/1 1; ACETAMINOPHEN 250 mg/1 1
INACTIVE INGREDIENTS: POLYDEXTROSE; STEARIC ACID; MICROCRYSTALLINE CELLULOSE; POVIDONE K30; HYPROMELLOSES; TALC; TITANIUM DIOXIDE; MALTODEXTRIN; STARCH, CORN; SILICON DIOXIDE; MEDIUM-CHAIN TRIGLYCERIDES

5004-Rugby

Drug Facts

Active ingredients (in each caplet)
Acetaminophen 250 mg
Aspirin 250 mg (NSAID*)
Caffeine 65 mg
*nonsteroidal anti-inflammatory drug

Purposes
Pain reliever
Pain reliever aid

Uses

■ temporarily relieves minor aches and pains due to:
■ headache

■ muscular aches

■ a cold

■ arthritis
■ toothache

■ premenstrual and menstrual cramps

WARNINGS

Reye’s syndrome: Children and teenagers who have or are recovering from chicken pox or flu-like symptoms should not use this product. When using this product, if changes in behavior with nausea and vomiting occur, consult a doctor because these
symptoms could be an early sign of Reye's syndrome, a rare but serious illness.
Allergy alert: Aspirin may cause a severe allergic reaction, which may include: ■ hives ■ facial swelling ■ shock ■ asthma (wheezing)
Allergy alert:Acetaminophen may cause severe skin reactions. Symptoms may include: ■ skin reddening ■ blisters ■ rash
If a skin reaction occurs, stop use and seek medical help right away.
Liver warning: This product contains acetaminophen. Severe liver damage may occur if you take: ■ with other drugs containing acetaminophen ■ more than 8 caplets in 24 hours, which is the maximum daily amount ■ 3 or more alcoholic drinks every day while
using this product
Stomach bleeding warning:This product contains an NSAID, which may cause severe stomach bleeding. The chance is higher if you: ■ are age 60 or older ■ take more or for a longer time than directed ■ have had stomach ulcers or bleeding problems
■ take a blood thinning (anticoagulant) or steroid drug ■ take other drugs containing prescription or nonprescription NSAIDs [aspirin, ibuprofen, naproxen, or others] ■ have 3 or more alcoholic drinks every day while using this product
Caffeine warning: The recommended dose of this product contains about as much caffeine as a cup of coffee. Limit the use of caffeine-containing medications, foods, or beverages while taking this product because too much caffeine may cause nervousness, irritability, sleeplessness, and, occasionally, rapid heartbeat.

Do not use

■ if you have ever had an allergic reaction to acetaminophen, aspirin, or any other pain reliever/fever reducer
■ with any other drug containing acetaminophen (prescription or nonprescription). If you are not sure whether a drug contains acetaminophen, ask a doctor or pharmacist.

Ask a doctor before use if

■ you have liver disease
■ stomach bleeding warning applies to you

■ you have a history of stomach problems, such as heartburn

■ you have high blood pressure, heart disease, liver cirrhosis, or kidney disease

■ you have asthma

■ you are taking a diuretic

Ask a doctor or pharmacist before use if you are
■ taking a prescription drug for diabetes, gout, or arthritis

■ taking any other drug or are under a doctor’s care for any serious condition

Stop use and ask a doctor if

■ you experience any of the following signs of stomach bleeding:

■ feel faint

■ have bloody or black stools

■ vomit blood

■ have stomach pain that does not get better

■ an allergic reaction occurs. Seek medical help right away.
■ ringing in the ears or loss of hearing occurs

■ pain gets worse or lasts for more than 10 days

■ fever gets worse or lasts for more than 3 days

■ painful area is red or swollen

■ any new symptoms appear.
These could be signs of a serious condition.

PREGNANCY OR BREAST FEEDING

If pregnant or breast-feeding, ask a health professional before use. It is especially important not to use aspirin during the last 3 months of pregnancy unless definitely directed to do so by a doctor because it may cause problems in the unborn child or complications during delivery.

Keep out of reach of children.

OVERDOSAGE

In case of accidental overdose, get medical help or contact a Poison Control Center (1-800-222-1222) right away. Prompt medical attention is critical for adults as well as for children even if you do not notice any signs or symptoms.

Directions

■ do not use more than directed
■ drink a full glass of water with each dose
■ adults and children 12 years and over:
■ take 2 caplets every 6 hours
■ do not take more than 8 caplets in 24 hours
■ children under 12 years: ask a doctor

Other information

■ Store in a dry place at 15° – 30°C (59° – 86°F)

■ use by expiration date on package

INACTIVE INGREDIENT

hypromellose, maltodextrin, microcrystalline cellulose, polydextrose, polyvinylpyrrolidone, pregelatinized starch, silica, starch, stearic acid, talc, titanium dioxide, triglycerides

Questions or comments?

(800) 231-4670

RETAIN THIS CARTON FOR COMPLETE PRODUCT INFORMATION

DISTRIBUTED BY: RUGBY® LABORATORIES
INDIANAPOLIS, IN 46268
(800) 616-2471 www.majorpharmaceuticals.com

†This product is not manufactured or distributed by GlaxoSmithKline, owner of the registered trademark Excedrin®

TAMPER EVIDENT: DO NOT USE IF IMPRINTED SAFETY SEAL UNDER CAP IS BROKEN OR MISSING